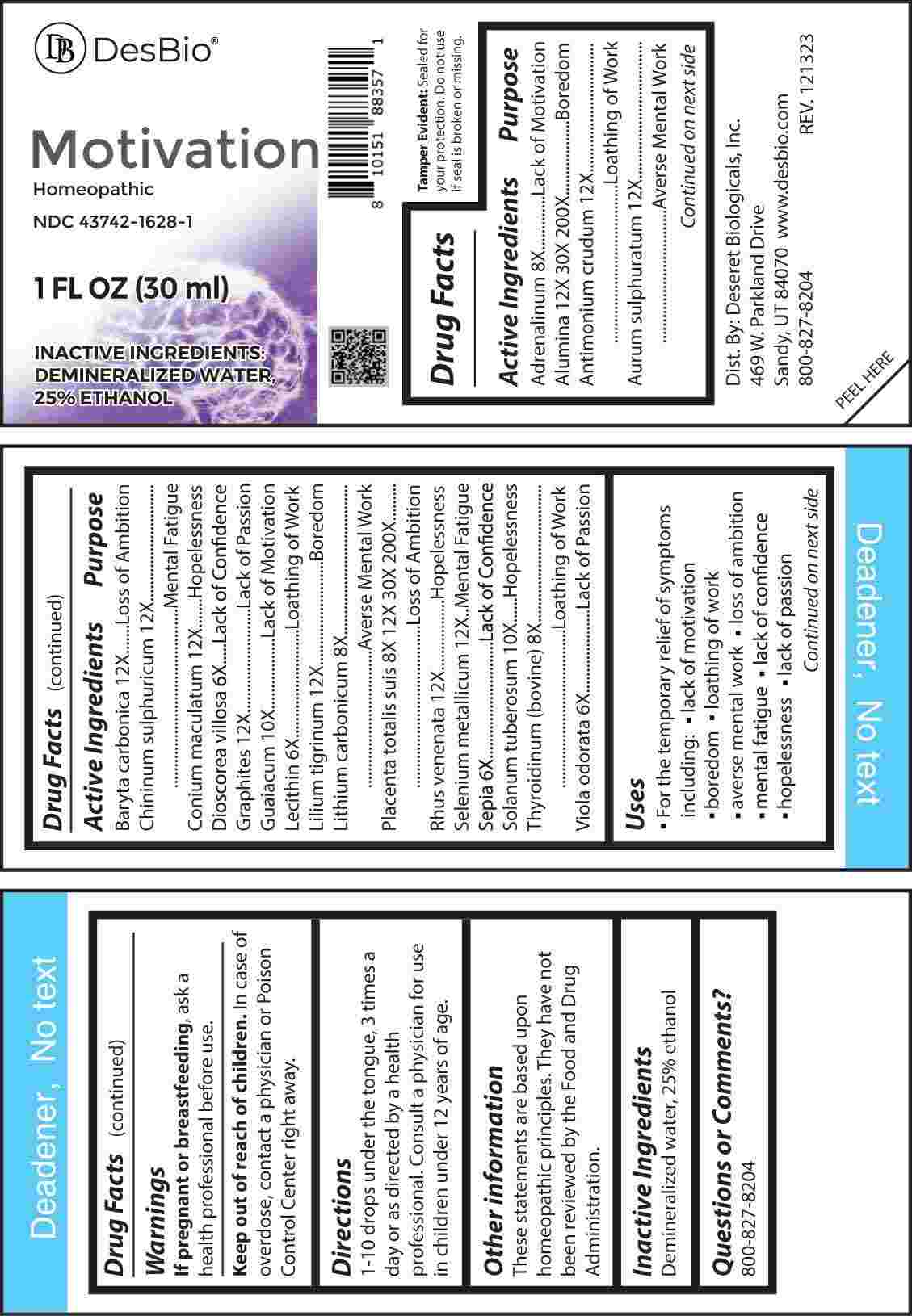 DRUG LABEL: Motivation
NDC: 43742-1628 | Form: LIQUID
Manufacturer: Deseret Biologicals, Inc.
Category: homeopathic | Type: HUMAN OTC DRUG LABEL
Date: 20240401

ACTIVE INGREDIENTS: DIOSCOREA VILLOSA TUBER 6 [hp_X]/1 mL; EGG PHOSPHOLIPIDS 6 [hp_X]/1 mL; SEPIA OFFICINALIS JUICE 6 [hp_X]/1 mL; VIOLA ODORATA WHOLE 6 [hp_X]/1 mL; EPINEPHRINE 8 [hp_X]/1 mL; LITHIUM CARBONATE 8 [hp_X]/1 mL; THYROID, BOVINE 8 [hp_X]/1 mL; SUS SCROFA PLACENTA 8 [hp_X]/1 mL; GUAIACUM OFFICINALE RESIN 10 [hp_X]/1 mL; SOLANUM TUBEROSUM WHOLE 10 [hp_X]/1 mL; ANTIMONY TRISULFIDE 12 [hp_X]/1 mL; GOLD MONOSULFIDE 12 [hp_X]/1 mL; BARIUM CARBONATE 12 [hp_X]/1 mL; QUININE SULFATE 12 [hp_X]/1 mL; CONIUM MACULATUM FLOWERING TOP 12 [hp_X]/1 mL; GRAPHITE 12 [hp_X]/1 mL; LILIUM LANCIFOLIUM WHOLE FLOWERING 12 [hp_X]/1 mL; TOXICODENDRON VERNIX LEAFY TWIG 12 [hp_X]/1 mL; SELENIUM 12 [hp_X]/1 mL; ALUMINUM OXIDE 12 [hp_X]/1 mL
INACTIVE INGREDIENTS: WATER; ALCOHOL

DRUG FACTS:

ACTIVE INGREDIENTS:

Adrenalinum 8X, Alumina 12X, 30X, 200X, Antimonium Crudum 12X, Aurum Sulphuratum 12X, Baryta Carbonica 12X, Chininum Sulphuricum 12X, Conium Maculatum 12X, Dioscorea Villosa 6X, Graphites 12X, Guaiacum 10X, Lecithin 6X, Lilium Tigrinum 12X, Lithium Carbonicum 8X, Placenta Totalis Suis 8X, 12X, 30X, 200X, Rhus Venenata 12X, Selenium Metallicum 12X, Sepia 6X, Solanum Tuberosum 10X, Thyroidinum (Bovine) 8X, Viola Odorata 6X.

PURPOSE:

Adrenalinum – Lack of Motivation, Alumina - Boredom, Antimonium Crudum – Loathing of Work, Aurum Sulphuratum – Averse Mental Work, Baryta Carbonica – Loss of Ambition, Chininum Sulphuricum – Mental Fatigue, Conium Maculatum - Hopelessness, Dioscorea Villosa – Lack of Confidence, Graphites – Lack of Passion, Guaiacum – Lack of Motivation, Lecithin – Loathing of Work, Lilium Tigrinum - Boredom, Lithium Carbonicum – Averse Mental Work, Placenta Totalis Suis – Loss of Ambition, Rhus Venenata - Hopelessness, Selenium Metallicum – Mental Fatigue, Sepia – Lack of Confidence, Solanum Tuberosum - Hopelessness, Thyroidinum (Bovine) – Loathing of Work, Viola Odorata – Lack of Passion

USES:

• For the temporary relief of symptoms including:

• lack of motivation • boredom • loathing of work

• averse mental work • loss of ambition • mental fatigue

• lack of confidence • hopelessness • lack of passion

These statements are based upon homeopathic principles. They have not been reviewed by the Food and Drug Administration.

WARNINGS:

If pregnant or breast-feeding, ask a health professional before use.

Keep out of reach of children. In case of overdose, contact a physician or Poison Control Center right away.

Tamper Evident: Sealed for your protection. Do not use if seal is broken or missing.

KEEP OUT OF REACH OF CHILDREN:

In case of overdose, contact a physician or Poison Control Center right away.

DIRECTIONS:

1-10 drops under the tongue, 3 times a day or as directed by a health professional. Consult a physician for use in children under 12 years of age.

INACTIVE INGREDIENTS:

Demineralized water, 25% ethanol

QUESTIONS:

Dist. By: Deseret Biologicals, Inc.
469 W. Parkland Drive
Sandy, UT 84070

www.desbio.com

800-827-8204

PACKAGE LABEL DISPLAY:

Des Bio

Motivation

Homeopathic

NDC 43742-1628-1

1 FL OZ (30 ml)